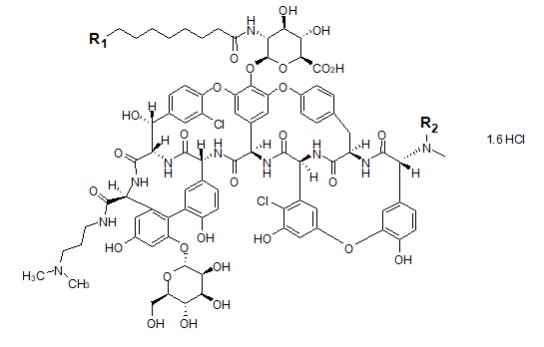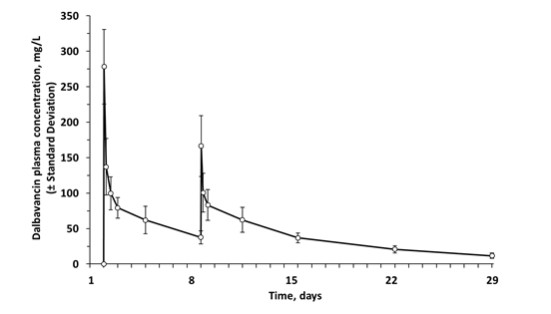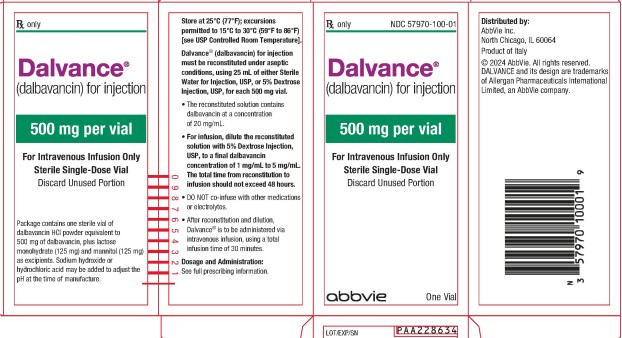 DRUG LABEL: DALVANCE
NDC: 57970-100 | Form: INJECTION, POWDER, FOR SOLUTION
Manufacturer: Allergan, Inc.
Category: prescription | Type: HUMAN PRESCRIPTION DRUG LABEL
Date: 20250113

ACTIVE INGREDIENTS: DALBAVANCIN HYDROCHLORIDE 500 mg/25 mL
INACTIVE INGREDIENTS: LACTOSE MONOHYDRATE 125 mg/25 mL; MANNITOL 125 mg/25 mL

HIGHLIGHTS OF PRESCRIBING INFORMATION

These highlights do not include all the information needed to use DALVANCE® safely and effectively. See full prescribing information for DALVANCE.
DALVANCE (dalbavancin) for injection, for intravenous use
Initial U.S. Approval: 2014

1 INDICATION AND USAGE

DALVANCE is a lipoglycopeptide antibacterial indicated for the treatment of adult and pediatric patients with acute bacterial skin and skin structure infections (ABSSSI) caused by designated susceptible strains of Gram-positive microorganisms. (1.1)

To reduce the development of drug-resistant bacteria and maintain the effectiveness of DALVANCE and other antibacterial drugs, DALVANCE should be used only to treat or prevent infections that are proven or strongly suspected to be caused by susceptible bacteria. (1.2)

2 DOSAGE AND ADMINISTRATION

Dosage in Adult Patients (2.1, 2.3):
Estimated Creatinine Clearance (CLcr) | Single Dose Regimen | Two-Dose Regimen
30 mL/min and above or on regular hemodialysis | 1,500 mg | 1,000 mg followed one week later by 500 mg
Less than 30 mL/min and not on regular hemodialysis | 1,125 mg | 750 mg followed one week later by 375 mg

- Administer by intravenous infusion over 30 minutes (2.1, 2.4)
- See Full Prescribing Information for instructions on reconstitution of lyophilized powder and preparation of injection (2.4).

Dosage in Pediatric Patients with CLcr 30 mL/min/1.73m^2
and above (2.2)
Age Range | Dosage (Single Dose Regimen)
Birth to less than 6 years | 22.5 mg/kg (maximum of 1,500 mg)
6 to less than 18 years | 18 mg/kg (maximum of 1,500 mg)

- Dosage adjustment in pediatric patients with CLcr less than 30 mL/min has not been studied.

3 DOSAGE FORMS AND STRENGTHS

For injection: 500 mg of lyophilized powder in a vial for reconstitution (3)

4 CONTRAINDICATIONS

Known hypersensitivity to dalbavancin (4)

5 WARNINGS AND PRECAUTIONS

- Serious hypersensitivity (anaphylactic) and skin reactions have been reported in patients treated with DALVANCE. If an allergic reaction occurs, discontinue treatment with DALVANCE and institute appropriate therapy for the allergic reaction. Carefully monitor patients with known hypersensitivity to glycopeptides. (5.1)
- Rapid intravenous infusion of DALVANCE can cause flushing of the upper body, urticaria, pruritus, rash, and/or back pain. Stopping or slowing the infusion may result in cessation of these reactions. (5.2)
- Alanine Aminotransferase (ALT) elevations with DALVANCE treatment were reported in clinical trials. (5.3, 6.1)
- Clostridioides difficile-associated diarrhea (CDAD) has been reported with nearly all systemic antibacterial agents, including DALVANCE. Evaluate if diarrhea occurs. (5.4)

6 ADVERSE REACTIONS

The most common adverse reactions occurring in >4% of adult patients treated with DALVANCE were nausea, headache, and diarrhea. The most common adverse reaction that occurred in >1% of pediatric patients was pyrexia. (6.1)

To report SUSPECTED ADVERSE REACTIONS, contact AbbVie Inc. at 1-800-678-1605 or FDA at 1-800-FDA-1088 or www.fda.gov/medwatch.

FULL PRESCRIBING INFORMATION

1 INDICATION AND USAGE

1.1 Acute Bacterial Skin and Skin Structure Infections

DALVANCE® is indicated for the treatment of adult and pediatric patients with acute bacterial skin and skin structure infections (ABSSSI) caused by designated susceptible strains of the following Gram-positive microorganisms: Staphylococcus aureus (including methicillin-susceptible and methicillin-resistant isolates), Streptococcus pyogenes, Streptococcus agalactiae, Streptococcus dysgalactiae, Streptococcus anginosus group (including S. anginosus, S. intermedius, S. constellatus) and Enterococcus faecalis (vancomycin susceptible isolates).

1.2 Usage

To reduce the development of drug-resistant bacteria and maintain the effectiveness of DALVANCE and other antibacterial agents, DALVANCE should be used only to treat or prevent infections that are proven or strongly suspected to be caused by susceptible bacteria. When culture and susceptibility information are available, they should be considered in selecting or modifying antibacterial therapy. In the absence of such data, local epidemiology and susceptibility patterns may contribute to the empiric selection of therapy.

2 DOSAGE AND ADMINISTRATION

2.1 Recommended Dosage Regimen in Adult Patients with CLcr 30 mL/min and Above

The recommended dosage regimen of DALVANCE in adult patients with CLcr 30 mL/min and above is 1,500 mg, administered either as a single dose regimen, or as a two-dose regimen of DALVANCE 1,000 mg followed one week later by 500 mg. Administer DALVANCE over 30 minutes by intravenous infusion. For adult patients with CLcr less than 30 mL/min, dosage adjustment is required [see Dosage and Administration (2.3) and Clinical Pharmacology (12.3)].

2.2 Recommended Dosage Regimen in Pediatric Patients with CLcr 30 mL/min/1.73m^2 and Above

The recommended dosage regimen of DALVANCE in pediatric patients with CLcr 30 mL/min/1.73m^2 and above is a single dose regimen based on the age and weight of the pediatric patient (Table 1). Administer DALVANCE over 30 minutes by intravenous infusion.

There is insufficient information to recommend dosage adjustment for pediatric patients younger than 18 years with CLcr less than 30 mL/min/1.73m^2 [see Use in Specific Populations (8.4) and Clinical Pharmacology (12.3)].

Table 1. Dosage of DALVANCE in Pediatric Patients with CLcr* 30 mL/min/1.73m2 and above
Age Range | Dosage (Single Dose Regimen)
Birth to less than 6 years | 22.5 mg/kg (maximum 1,500 mg)
6 to less than 18 years | 18 mg/kg (maximum 1,500 mg)

*Estimate CLcr or glomerular filtration rate (GFR) using an age-appropriate equation accepted for pediatric patients (birth to less than 18 years old) to define renal function impairment.

2.3 Dosage Adjustments in Adult Patients with CLcr less than 30 mL/min

In adult patients with renal impairment whose known CLcr is less than 30 mL/min and who are not receiving regularly scheduled hemodialysis, the recommended dosage regimen of DALVANCE is 1,125 mg, administered either as a single dose regimen, or as a two-dose regimen of DALVANCE 750 mg followed one week later by 375 mg.

No dosage adjustment is recommended for adult patients receiving regularly scheduled hemodialysis, and DALVANCE can be administered without regard to the timing of hemodialysis [see Use in Specific Populations (8.6) and Clinical Pharmacology (12.3)].

2.4 Preparation and Administration

DALVANCE (dalbavancin) for injection must be reconstituted with either Sterile Water for Injection, USP, or 5% Dextrose Injection, USP, and subsequently diluted only with 5% Dextrose Injection, USP, to a final concentration of 1 mg/mL to 5 mg/mL.

Parenteral drug products should be inspected visually for particulate matter and discoloration prior to administration, whenever solution and container permit.

Reconstitution: DALVANCE must be reconstituted under aseptic conditions, using 25 mL of either Sterile Water for Injection, USP, or 5% Dextrose Injection, USP, for each 500 mg vial. To avoid foaming, alternate between gentle swirling and inversion of the vial until its contents are completely dissolved. Do not shake. The reconstituted vial contains 20 mg/mL dalbavancin as a clear, colorless to yellow solution.

Reconstituted vials may be stored either refrigerated at 2°C to 8°C (36°F to 46°F), or at controlled room temperature 20°C to 25°C (68°F to 77°F). Do not freeze.

Dilution:

Adult Patients: Aseptically transfer the required dose of reconstituted DALVANCE solution from the vial(s) to an intravenous bag or bottle containing 5% Dextrose Injection, USP. The diluted solution must have a final dalbavancin concentration of 1 mg/mL to 5 mg/mL. Discard any unused portion of the reconstituted solution.

Pediatric Patients: For pediatric patients, the dose of DALVANCE will vary according to the age and weight of the child up to a maximum of 1,500 mg [see Dosage and Administration (2.2)]. Aseptically transfer the required dose of reconstituted DALVANCE solution, based on the child’s weight, from the vial(s) to an intravenous bag or bottle containing 5% Dextrose Injection, USP. The diluted solution must have a final dalbavancin concentration of 1 mg/mL to 5 mg/mL. Discard any unused portion of the reconstituted solution.

Once diluted into an intravenous bag or bottle as described above, DALVANCE may be stored either refrigerated at 2°C to 8°C (36°F to 46°F) or at a controlled room temperature of 20°C to 25°C (68°F to 77°F). Do not freeze.

The total time from reconstitution to dilution to administration should not exceed 48 hours.

Like all parenteral drug products, diluted DALVANCE should be inspected visually for particulate matter prior to infusion. If particulate matter is identified, do not use.

Administration: After reconstitution and dilution, administer DALVANCE via intravenous infusion, using a total infusion time of 30 minutes.

Do not co-infuse DALVANCE with other medications or electrolytes. Saline-based infusion solutions may cause precipitation and should not be used. The compatibility of reconstituted DALVANCE with intravenous medications, additives, or substances other than 5% Dextrose Injection, USP has not been established.

If a common intravenous line is being used to administer other drugs in addition to DALVANCE, the line should be flushed before and after each DALVANCE infusion with 5% Dextrose Injection, USP.

3 DOSAGE FORMS AND STRENGTHS

DALVANCE (dalbavancin) for injection is supplied as a white/off-white to pale yellow lyophilized sterile powder for reconstitution in a single-dose clear glass vial containing dalbavancin hydrochloride equivalent to 500 mg of dalbavancin.

4 CONTRAINDICATIONS

DALVANCE is contraindicated in patients with known hypersensitivity to dalbavancin.

5 WARNINGS AND PRECAUTIONS

5.1 Hypersensitivity Reactions

Serious hypersensitivity (anaphylactic) and skin reactions have been reported in patients treated with DALVANCE. If an allergic reaction to DALVANCE occurs, discontinue treatment with DALVANCE and institute appropriate therapy for the allergic reaction. Before using DALVANCE, inquire carefully about previous hypersensitivity reactions to other glycopeptides. Due to the possibility of cross-sensitivity, carefully monitor for signs of hypersensitivity during treatment with DALVANCE in patients with a history of glycopeptide allergy [see Patient Counseling Information (17)].

5.2 Infusion-Related Reactions

DALVANCE is administered via intravenous infusion, using a total infusion time of 30 minutes to minimize the risk of infusion-related reactions. Rapid intravenous infusions of DALVANCE can cause flushing of the upper body, urticaria, pruritus, rash, and/or back pain. Stopping or slowing the infusion may result in cessation of these reactions.

5.3 Hepatic Effects

In Phase 2 and 3 clinical trials, more DALVANCE than comparator-treated subjects with normal baseline transaminase levels had post-baseline alanine aminotransferase (ALT) elevation greater than 3 times the upper limit of normal (ULN). Overall, abnormalities in liver tests (ALT, AST, bilirubin) were reported with similar frequency in the DALVANCE and comparator arms [see Adverse Reactions (6.1)].

5.4 Clostridioides difficile-Associated Diarrhea

Clostridioides difficile-associated diarrhea (CDAD) has been reported in users of nearly all systemic antibacterial drugs, including DALVANCE, with severity ranging from mild diarrhea to fatal colitis. Treatment with antibacterial agents can alter the normal flora of the colon, and may permit overgrowth of C. difficile.

C. difficile produces toxins A and B which contribute to the development of CDAD. Hypertoxin-producing strains of C. difficile cause increased morbidity and mortality, as these infections can be refractory to antibacterial therapy and may require colectomy. CDAD must be considered in all patients who present with diarrhea following antibacterial use. Careful medical history is necessary because CDAD has been reported to occur more than 2 months after the administration of antibacterial agents.

If CDAD is suspected or confirmed, ongoing antibacterial use not directed against C. difficile should be discontinued, if possible. Appropriate measures such as fluid and electrolyte management, protein supplementation, antibacterial treatment of C. difficile, and surgical evaluation should be instituted as clinically indicated.

5.5 Development of Drug-Resistant Bacteria

Prescribing DALVANCE in the absence of a proven or strongly suspected bacterial infection or a prophylactic indication is unlikely to provide benefit to the patient and increases the risk of the development of drug-resistant bacteria.

6 ADVERSE REACTIONS

The following clinically significant adverse reactions are also discussed elsewhere in the labeling:

- Hypersensitivity Reactions [see Warnings and Precautions (5.1)]
- Infusion Related Reactions [see Warnings and Precautions (5.2)]
- Hepatic Effects [see Warnings and Precautions (5.3)]
- Clostridioides difficile-associated Diarrhea [see Warnings and Precautions (5.4)]

6.1 Clinical Trials Experience

Because clinical trials are conducted under widely varying conditions, adverse reaction rates observed in clinical trials of DALVANCE cannot be directly compared to rates in the clinical trials of another drug and may not reflect rates observed in practice.

Clinical Trials Experience in Adult Patients

Adverse reactions were evaluated for 2,473 patients treated with DALVANCE: 1,778 patients were treated with DALVANCE in seven Phase 2/3 trials comparing DALVANCE to comparator antibacterial drugs and 695 patients were treated with DALVANCE in one Phase 3 trial comparing DALVANCE single and two-dose regimens. The median age of patients treated with DALVANCE was 48 years, ranging between 16 and 93 years. Patients treated with DALVANCE were predominantly male (59.5%) and White (81.2%).

Serious Adverse Reactions and Adverse Reactions Leading to Discontinuation

Serious adverse reactions occurred in 121/2,473 (4.9%) of patients treated with any regimen of DALVANCE. In the Phase 2/3 trials comparing DALVANCE to comparator, serious adverse reactions occurred in 109/1,778 (6.1%) of patients in the DALVANCE group and 80/1,224 (6.5%) of patients in the comparator group. In a Phase 3 trial comparing DALVANCE single and two-dose regimens, serious adverse reactions occurred in 7/349 (2.0%) of patients in the DALVANCE single dose group and 5/346 (1.4%) of patients in the DALVANCE two-dose group. DALVANCE was discontinued due to an adverse reaction in 64/2,473 (2.6%) patients treated with any regimen of DALVANCE. In the Phase 2/3 trials comparing DALVANCE to comparator, DALVANCE was discontinued due to an adverse reaction in 53/1,778 (3.0%) of patients in the DALVANCE group and 35/1,224 (2.9%) of patients in the comparator group. In a Phase 3 trial comparing DALVANCE single and two-dose regimens, DALVANCE was discontinued due to an adverse reaction in 6/349 (1.7%) of patients in the DALVANCE single dose group and 5/346 (1.4%) of patients in the DALVANCE two-dose group.

Most Common Adverse Reactions

The most common adverse reactions in patients treated with DALVANCE in Phase 2/3 trials were nausea (5.5%), headache (4.7%), and diarrhea (4.4%). The median duration of adverse reactions was 3.0 days in patients treated with DALVANCE. In the Phase 2/3 trials comparing DALVANCE to comparator, the median duration of adverse reactions was 3.0 days for patients in the DALVANCE group and 4.0 days in patients in the comparator group. In a Phase 3 trial comparing DALVANCE single and two-dose regimens, the median duration of adverse reactions was 3.0 days for patients in the DALVANCE single and two-dose group.

Table 2 lists selected adverse reactions occurring in 2% or more of patients treated with DALVANCE in Phase 2/3 clinical trials.

Table 2. Selected Adverse Reactions Occurring in ≥ 2% of Patients Receiving DALVANCE in Phase 2/3 Trials
(Number (%) of Patients)
Adverse Reactions | DALVANCE | Comparator*
 | (N = 1,778) | (N = 1,224)
Nausea | 98 (5.5) | 78 (6.4)
Diarrhea | 79 (4.4) | 72 (5.9)
Headache | 83 (4.7) | 59 (4.8)
Vomiting | 50 (2.8) | 37 (3)
Rash | 48 (2.7) | 30 (2.4)
Pruritus | 38 (2.1) | 41 (3.3)
* Comparators included linezolid, cefazolin, cephalexin, and vancomycin.

In the Phase 3 trial comparing the single and two-dose regimen of DALVANCE, the adverse reaction that occurred in 2% or more of patients treated with DALVANCE was nausea (3.4% in the DALVANCE single dose group and 2% in the DALVANCE two-dose group).

The following selected adverse reactions were reported in DALVANCE treated patients at a rate of less than 2% in these clinical trials:

Blood and lymphatic system disorders: anemia, hemorrhagic anemia, leucopenia, neutropenia, thrombocytopenia, petechiae, eosinophilia, thrombocytosis

Gastrointestinal disorders: gastrointestinal hemorrhage, melena, hematochezia, abdominal pain

General disorders and administration site conditions: infusion-related reactions

Hepatobiliary disorders: hepatotoxicity

Immune system disorders: anaphylactic reaction

Infections and infestations: Clostridioides difficile colitis, oral candidiasis, vulvovaginal mycotic infection

Investigations: hepatic transaminases increased, blood alkaline phosphatase increased, international normalized ratio increased, blood lactate dehydrogenase increased, gamma-glutamyl transferase increased

Metabolism and nutrition disorders: hypoglycemia

Nervous system disorders: dizziness

Respiratory, thoracic and mediastinal disorders: bronchospasm

Skin and subcutaneous tissue disorders: rash, pruritus, urticaria

Vascular disorders: flushing, phlebitis, wound hemorrhage, spontaneous hematoma

Alanine Aminotransferase (ALT) Elevations

Among patients with normal baseline ALT levels treated with DALVANCE 17 (0.8%) had post baseline ALT elevations greater than 3 times the upper limit of normal (ULN) including five subjects with post-baseline ALT values greater than 10 times ULN. Among patients with normal baseline ALT levels treated with non-DALVANCE comparators 2 (0.2%) had post-baseline ALT elevations greater than 3 times the upper limit of normal. Fifteen of the 17 patients treated with DALVANCE and one comparator patient had underlying conditions which could affect liver enzymes, including chronic viral hepatitis, history of alcohol abuse and metabolic syndrome. In addition, one DALVANCE-treated subject in a Phase 1 trial had post-baseline ALT elevations greater than 20 times ULN. ALT elevations were reversible in all subjects with follow-up assessments. No comparator-treated subject with normal baseline transaminases had post-baseline ALT elevation greater than 10 times ULN.

Clinical Trials Experience in Pediatric Patients

Adverse reactions were evaluated in one Phase 3 pediatric clinical trial which included 161 pediatric patients from birth to less than 18 years of age with ABSSSI treated with DALVANCE (83 patients treated with a single dose of DALVANCE and 78 patients treated with a two-dose regimen of DALVANCE) and 30 patients treated with comparator agents for a treatment period up to 14 days. The median age of pediatric patients treated with DALVANCE was 9 years, ranging from birth to <18 years. The majority of patients were male (62.3%) and White (89.0%).

The safety findings of DALVANCE in pediatric patients were similar to those observed in adults.

Serious Adverse Reactions and Adverse Reactions Leading to Discontinuation

Serious adverse reactions (SARs) occurred in 3/161 (1.9%) of patients treated with DALVANCE, all in the single-dose arm. There were no adverse reactions leading to DALVANCE discontinuation.

Most Common Adverse Reactions

Most common adverse reaction occurring in more than 1% of pediatric patients 2/161 (1.2%) was pyrexia.

Other Adverse Reactions

The following selected adverse reactions were reported in DALVANCE-treated patients at a rate of less than 1% in this pediatric clinical trial:

Gastrointestinal disorders: diarrhea

Nervous system disorders: dizziness

Skin and subcutaneous tissue disorders: pruritus

6.2 Post Marketing Experience

The following adverse reaction has been identified during post-approval use of dalbavancin. Because the reaction is reported voluntarily from a population of uncertain size, it is not possible to reliably estimate the frequency or establish a causal relationship to drug exposure.

General disorders and administration site conditions: Back pain as an infusion-related reaction [See Warnings and Precautions (5.2)].

7 DRUG INTERACTIONS

7.1 Drug-Laboratory Test Interactions

Drug-laboratory test interactions have not been reported. DALVANCE at therapeutic concentrations does not artificially prolong prothrombin time (PT) or activated partial thromboplastin time (aPTT).

7.2 Drug-Drug Interactions

No clinical drug-drug interaction studies have been conducted with DALVANCE. There is minimal potential for drug-drug interactions between DALVANCE and cytochrome P450 (CYP450) substrates, inhibitors, or inducers [see Clinical Pharmacology (12.3)].

8 USE IN SPECIFIC POPULATIONS

8.1 Pregnancy

Risk Summary

There are no adequate and well-controlled studies with DALVANCE use in pregnant women to evaluate for a drug-associated risk of major birth defects, miscarriage or adverse developmental outcomes.

No treatment-related malformations or embryo-fetal toxicity were observed in pregnant rats or rabbits at clinically relevant exposures of dalbavancin. Treatment of pregnant rats with dalbavancin at 3.5 times the human dose on an exposure basis during early embryonic development and from implantation to the end of lactation resulted in delayed fetal maturation and increased fetal loss, respectively [see Data].

The estimated background risk of major birth defects and miscarriage for the indicated population is unknown. All pregnancies have a background risk of birth defect, loss, or other adverse outcomes. In the U.S. general population, the estimated background risk of major birth defects and miscarriage in clinically recognized pregnancies is 2% to 4% and 15% to 20%, respectively.

Data

Animal Data

No evidence of embryo or fetal toxicity was found in the rat or rabbit at a dose of 15 mg/kg/day (1.2 and 0.7 times the human dose on an exposure basis, respectively). Delayed fetal maturation was observed in the rat at a dose of 45 mg/kg/day (3.5 times the human dose on an exposure basis).

In a rat prenatal and postnatal development study, increased embryo lethality and increased offspring deaths during the first week post-partum were observed at a dose of 45 mg/kg/day (3.5 times the human dose on an exposure basis).

8.2 Lactation

Risk Summary

There are no data on the presence of dalbavancin or its metabolite in human milk, the effects on the breast-fed child, or the effects on milk production. Dalbavancin is excreted in the milk of lactating rats. When a drug is present in animal milk, it is likely that the drug will be present in human milk.

The developmental and health benefits of breastfeeding should be considered along with the mother’s clinical need for DALVANCE and any potential adverse effects on the breast-fed child from DALVANCE or from the underlying maternal condition.

8.4 Pediatric Use

The safety and effectiveness of DALVANCE for the treatment of ABSSSI has been established in pediatric patients aged birth to less than 18 years. Use of DALVANCE for this indication is supported by evidence from adequate and well-controlled studies in adults with additional pharmacokinetic and safety data in pediatric patients aged birth to less than 18 years [see Adverse Reactions (6.1), Clinical Pharmacology (12.3), and Clinical Studies (14.1)].

There is insufficient information to recommend dosage adjustment for pediatric patients with ABSSSI and CLcr less than 30 mL/min/1.73m^2 [see Dosage and Administration (2.2)].

8.5 Geriatric Use

Of the 2,473 patients treated with DALVANCE in Phase 2 and 3 clinical trials, 403 patients (16.3%) were 65 years of age or older. The efficacy and tolerability of DALVANCE were similar to comparator regardless of age. The pharmacokinetics of DALVANCE was not significantly altered with age; therefore, no dosage adjustment is necessary based on age alone.

DALVANCE is substantially excreted by the kidney, and the risk of adverse reactions may be greater in patients with impaired renal function. Because elderly patients are more likely to have decreased renal function, care should be taken in dose selection in this age group.

8.6 Renal Impairment

In patients with renal impairment whose known CLcr is less than 30 mL/min and who are not receiving regularly scheduled hemodialysis, the recommended regimen for DALVANCE is 1,125 mg, administered as a single dose, or 750 mg followed one week later by 375 mg. No dosage adjustment is recommended for patients receiving regularly scheduled hemodialysis, and DALVANCE can be administered without regard to the timing of hemodialysis. There is insufficient information to recommend dosage adjustment for pediatric patients younger than 18 years with CLcr less than 30 mL/min/1.73m^2 [see Dosage and Administration (2.3), Clinical Pharmacology (12.3)].

8.7 Hepatic Impairment

No dosage adjustment of DALVANCE is recommended for patients with mild hepatic impairment (Child-Pugh Class A). Caution should be exercised when prescribing DALVANCE to patients with moderate or severe hepatic impairment (Child-Pugh Class B or C) as no data are available to determine the appropriate dosing in these patients [see Clinical Pharmacology (12.3)].

10 OVERDOSAGE

Specific information is not available on the treatment of overdose with DALVANCE, as dose-limiting toxicity has not been observed in clinical studies. In Phase 1 studies, healthy volunteers have been administered cumulative doses of up to 4,500 mg over a period of up to 8 weeks (not an approved dosing regimen), with no signs of toxicity or laboratory results of clinical concern.

Treatment of overdose with DALVANCE should consist of observation and general supportive measures. Although no information is available specifically regarding the use of hemodialysis to treat overdose, in a Phase 1 study in patients with renal impairment less than 6% of the recommended dalbavancin dose was removed [see Clinical Pharmacology (12.3)].

11 DESCRIPTION

DALVANCE (dalbavancin) for injection is a lipoglycopeptide antibacterial synthesized from a fermentation product of Nonomuraea species.

Dalbavancin is a mixture of five closely related active homologs (A0, A1, B0, B1, and B2); the component B0 is the major component of dalbavancin. The homologs share the same core structure and differ in the fatty acid side chain of the N-acylaminoglucuronic acid moiety (R1) structure and/or the presence of an additional methyl group (R2) on the terminal amino group (shown in the Figure 1 and Table 3 below).

Figure 1. Dalbavancin Structural Formula

Table 3. Substitution Patterns for Dalbavancin API Homologs
Dalbavancin | R1 | R2 | Molecular Formula | Molecular Weight*
A0 | CH(CH3)2 | H | C87H98N10O28Cl2 · 1.6 HCl | 1,802.7
A1 | CH2CH2CH3 | H | C87H98N10O28Cl2 · 1.6 HCl | 1,802.7
B0 | CH2CH(CH3)2 | H | C88H100N10O28Cl2 · 1.6 HCl | 1,816.7
B1 | CH2CH2CH2CH3 | H | C88H100N10O28Cl2 · 1.6 HCl | 1,816.7
B2 | CH2CH(CH3)2 | CH3 | C89H102N10O28Cl2 · 1.6 HCl | 1,830.7

*Anhydrous free base

The B0 INN chemical name is: 5,31-dichloro-38-de(methoxycarbonyl)-7-demethyl-19-deoxy-56-O-[2-deoxy-2-[(10-methylundecanoyl)amino]-β-D-glucopyranuronosyl]-38-[[3-(dimethylamino)propyl] carbamoyl]-42-O-α-D-mannopyranosyl-15-N-methyl(ristomycin A aglycone) hydrochloride.

DALVANCE is supplied in clear glass vials as a sterile, lyophilized, preservative-free, white to off-white to pale yellow solid. Each vial contains dalbavancin HCl equivalent to 500 mg of dalbavancin as the free base, plus lactose monohydrate (125 mg) and mannitol (125 mg) as excipients. Sodium hydroxide or hydrochloric acid may be added to adjust the pH at the time of manufacture. The powder is to be reconstituted and further diluted for IV infusion [see Dosage and Administration (2.4), How Supplied/Storage and Handling (16)].

12 CLINICAL PHARMACOLOGY

12.1 Mechanism of Action

Dalbavancin is an antibacterial drug [see Microbiology (12.4)].

12.2 Pharmacodynamics

The antibacterial activity of dalbavancin appears to best correlate with the ratio of area under the concentration-time curve to minimal inhibitory concentration (AUC/MIC) for Staphylococcus aureus based on animal models of infection. An exposure-response analysis of a single study in patients with complicated skin and skin structure infections supports the two-dose regimen [see Dosage and Administration (2.1), Clinical Pharmacology (12.3)].

Cardiac Electrophysiology

In a randomized, positive- and placebo-controlled, thorough QT/QTc study, 200 healthy subjects received dalbavancin 1,000 mg IV, dalbavancin 1,500 mg IV, oral moxifloxacin 400 mg, or placebo. Neither dalbavancin 1,000 mg nor dalbavancin 1,500 mg had any clinically relevant adverse effect on cardiac repolarization.

12.3 Pharmacokinetics

General Pharmacokinetic Properties

Dalbavancin pharmacokinetic parameters have been characterized in healthy subjects, patients, and specific populations. Pharmacokinetic parameters following administration of single intravenous 1,000 mg and 1,500 mg doses were as shown in Table 4. The pharmacokinetics of dalbavancin can be described using a three-compartment model.

Table 4. Dalbavancin Pharmacokinetic Parameters in Healthy Subjects
Parameter | Single 1,000 mg Dose | Single 1,500 mg Dose
Cmax (mg/L) | 287 (13.9)^1 | 423 (13.2)^4
AUC0-24 (mg•h/L) | 3,185 (12.8)^1 | 4,837 (13.7)^4
AUC0-Day7 (mg•h/L) | 11,160 (41.1)^2 | ND
AUC0-inf (mg•h/L) | 23,443 (40.9)^2 | ND
Terminal t½ (h) | 346 (16.5)^2,3 | ND
CL (L/h) | 0.0513 (46.8)^2 | ND
All values are presented as mean (% coefficient of variation)
^1 Data from 50 healthy subjects.
^2 Data from 12 healthy subjects.
^3 Based upon population pharmacokinetic analyses of data from patients, the effective half-life is approximately 8.5 days (204 hours).
^4 Data from 49 healthy subjects.
Abbreviation: ND – not determined

In healthy subjects, dalbavancin AUC0-24h and Cmax both increased proportionally to dose following single IV dalbavancin doses ranging from 140 mg to 1,500 mg, indicating linear pharmacokinetics.

The mean plasma concentration-time profile for dalbavancin following the recommended two-dose regimen of 1,000 mg followed one week later by 500 mg is shown in Figure 2.

Figure 2. Mean (± standard deviation) dalbavancin plasma concentrations versus time in healthy subjects (n=10) following IV administration over 30 minutes of 1,000 mg dalbavancin (Day 1) and 500 mg dalbavancin (Day 8).

No apparent accumulation of dalbavancin was observed following multiple IV infusions administered once weekly for up to eight weeks, with 1,000 mg on Day 1 followed by up to seven weekly 500 mg doses, in healthy adults with normal renal function.

Distribution

Dalbavancin is reversibly bound to human plasma proteins, primarily to albumin. The plasma protein binding of dalbavancin is approximately 93% and is not altered as a function of drug concentration, renal impairment, or hepatic impairment. The mean concentrations of dalbavancin achieved in skin blister fluid remain above 30 mg/L up to 7 days (approximately 146 hours) post dose, following 1,000 mg IV dalbavancin. The mean ratio of the AUC0-144 hrs in skin blister fluid/AUC0-144 hrs in plasma is 0.60 (range 0.44 to 0.64).

Metabolism

In vitro studies using human microsomal enzymes and hepatocytes indicate that dalbavancin is not a substrate, inhibitor, or inducer of CYP450 isoenzymes. A minor metabolite of dalbavancin (hydroxy-dalbavancin) has been observed in the urine of healthy subjects. Quantifiable concentrations of the hydroxy-dalbavancin metabolite have not been observed in human plasma (lower limit of quantitation = 0.4 µg/mL) [see Drug Interactions (7.2)].

Excretion

Following administration of a single 1,000 mg dose in healthy subjects, 20% of the dose was excreted in feces through 70 days post dose. An average of 33% of the administered dalbavancin dose was excreted in urine as unchanged dalbavancin and approximately 12% of the administered dose was excreted in urine as the metabolite hydroxy-dalbavancin through 42 days post dose.

Specific Populations

Renal Impairment

The pharmacokinetics of dalbavancin were evaluated in 28 subjects with varying degrees of renal impairment and in 15 matched control subjects with normal renal function.

Following a single dose of 500 mg or 1,000 mg dalbavancin, the mean plasma clearance (CLT) was reduced 11%, 35%, and 47% in subjects with CLcr 50 to 79 mL/min, CLcr 30 to 49 mL/min, and CLcr less than 30 mL/min, respectively, compared to subjects with normal renal function. The clinical significance of the decrease in mean plasma CLT, and the associated increase in AUC0-∞ noted in these pharmacokinetic studies of dalbavancin in subjects with CLcr less than 30 mL/min has not been established [see Dosage and Administration (2.3), Use in Specific Populations (8.6)].

Dalbavancin pharmacokinetic parameters in subjects with end-stage renal disease receiving regularly scheduled hemodialysis (three times/week) are similar to those observed in subjects with mild to moderate renal impairment, and less than 6% of an administered dose is removed after three hours of hemodialysis.

Therefore, no dosage adjustment is recommended for patients receiving regularly scheduled hemodialysis, and dalbavancin may be administered without regard to the timing of hemodialysis in such patients [see Dosage and Administration (2.1), Overdosage (10)].

Hepatic Impairment

The pharmacokinetics of dalbavancin were evaluated in 17 subjects with mild, moderate, or severe hepatic impairment (Child-Pugh class A, B or C) and compared to those in nine matched healthy subjects with normal hepatic function. The mean AUC0-336 hrs was unchanged in subjects with mild hepatic impairment compared to subjects with normal hepatic function; however, the mean AUC0-336 hrs decreased 28% and 31% in subjects with moderate and severe hepatic impairment respectively, compared to subjects with normal hepatic function. The clinical significance of the decreased AUC0-336 hrs in subjects with moderate and severe hepatic function is unknown.

No dosage adjustment is recommended for patients with mild hepatic impairment. Caution should be exercised when prescribing dalbavancin to patients with moderate or severe hepatic impairment as no data are available to determine the appropriate dosing.

Gender

Clinically significant gender-related differences in dalbavancin pharmacokinetics have not been observed either in healthy subjects or in patients with infections. No dosage adjustment is recommended based on gender.

Geriatric Patients

Clinically significant age-related differences in dalbavancin pharmacokinetics have not been observed in patients with infections. No dosage adjustment is recommended based solely on age.

Pediatric Patients

The pharmacokinetics of dalbavancin has been evaluated in 211 individual pediatric patients [4 days to 17.9 years of age, including a preterm neonate (gestational age 36 weeks; n=1) and term neonates (gestational age 37 to 40 weeks; n=4)] with CLcr 30 mL/min/1.73 m^2 and above. There is insufficient information to assess the exposure of DALVANCE in the pediatric patients with CLcr less than 30 mL/min/1.73 m^2. No clinically important differences in drug exposure between pediatric age groups (including preterm neonates) and adults are expected following administration of the age-dependent recommended single dose of DALVANCE. The median plasma AUC from 0 to 120 hours (AUC0-120h) of dalbavancin in pediatric patient age groups from term neonates at birth to less than 18 years is expected to be comparable to that in adult patients (AUC0-120h, 10,400 mg*h/L). The expected median plasma AUC0-120h of dalbavancin in preterm neonates at birth (gestational age 26 weeks to <37 weeks) was approximately 62% of that in adult patients. The expected median maximum plasma concentrations (Cmax) of dalbavancin for pediatric patient age groups ranged between approximately 53% to 73% of that in adult patients (Cmax, 412 mg/L). However, in all pediatric age groups, the percentage of patients attaining PK/PD targets related to in vivo drug activity were above 90% or higher for MICs up to 0.25 mg/L.

Drug Interactions

Nonclinical studies demonstrated that dalbavancin is not a substrate, inhibitor, or inducer of CYP450 isoenzymes. In a population pharmacokinetic analysis, dalbavancin pharmacokinetics were not affected by co-administration with known CYP450 substrates, inducers or inhibitors, nor by individual medications including acetaminophen, aztreonam, fentanyl, metronidazole, furosemide, proton pump inhibitors (omeprazole, esomeprazole, pantoprazole, lansoprazole), midazolam, and simvastatin.

12.4 Microbiology

Mechanism of Action

Dalbavancin, a semisynthetic lipoglycopeptide, interferes with cell wall synthesis by binding to the D-alanyl-D-alanine terminus of the stem pentapeptide in nascent cell wall peptidoglycan, thus preventing cross-linking. Dalbavancin is bactericidal in vitro against Staphylococcus aureus and Streptococcus pyogenes at concentrations similar to those sustained throughout treatment in humans treated according to the recommended dosage regimen.

Resistance

The development of bacterial isolates resistant to dalbavancin has not been observed, either in vitro, in studies using serial passage, or in animal infection experiments.

Interaction with Other Antimicrobials

When tested in vitro, dalbavancin demonstrated synergistic interactions with oxacillin and did not demonstrate antagonistic or synergistic interactions with any of the following antibacterial agents of various classes: gentamicin, vancomycin, levofloxacin, clindamycin, quinupristin/dalfopristin, linezolid, aztreonam, rifampin or daptomycin. The clinical significance of these in vitro findings is unknown.

Antimicrobial Activity

Dalbavancin has been shown to be active against the following microorganisms, both in vitro and in clinical infections [see Indications and Usage (1)].

Aerobic bacteria

Gram-positive bacteria

Staphylococcus aureus (including methicillin-resistant isolates)

Streptococcus pyogenes

Streptococcus agalactiae

Streptococcus dysgalactiae

Streptococcus anginosus group (including S. anginosus, S. intermedius, S. constellatus)

Enterococcus faecalis (vancomycin-susceptible isolates only)

The following in vitro data are available, but their clinical significance is unknown. At least 90 percent of the following bacteria exhibit an in vitro minimum inhibitory concentration (MIC) less than or equal to the susceptible breakpoint for dalbavancin against isolates of similar genus or organism group. However, the efficacy of dalbavancin in treating clinical infections caused by these bacteria has not been established in adequate well-controlled clinical trials.

Aerobic bacteria

Gram-positive bacteria

Enterococcus faecium (vancomycin-susceptible isolates only)

Susceptibility Testing

For specific information regarding susceptibility test interpretive criteria and associated test methods and quality control standards recognized by FDA for this drug, please see: https://www.fda.gov/STIC.

13 NONCLINICAL TOXICOLOGY

13.1 Carcinogenesis, Mutagenesis, Impairment of Fertility

Carcinogenesis

Long-term studies in animals to determine the carcinogenic potential of dalbavancin have not been conducted.

Mutagenesis

Dalbavancin was not genotoxic in a bacterial reverse mutation (Ames) assay, a mammalian HGPRT gene mutation assay, an in vitro chromosome aberration assay in Chinese Hamster Ovary cells, or an in vivo mouse micronucleus assay.

Impairment of Fertility

Impaired fertility in the rat was not observed at a dose of 15 mg/kg/day (1.2 times the human dose on an exposure basis). Reductions in male and female fertility and increased embryo resorptions occurred at a dose of 45 mg/kg/day (3.5 times the human dose on an exposure basis), at which signs of parental toxicity were also observed.

13.2 Animal Toxicology and/or Pharmacology

Increases in serum levels of liver enzymes (ALT, AST), associated with microscopic findings in the liver were noted in toxicology studies in rats and dogs where dalbavancin was administered daily for 28 to 90 days. Hepatocellular necrosis was observed in dogs dosed at ≥10 mg/kg/day for longer than 2 months, i.e., at approximately 5 to 7 times the expected human dose on an exposure basis. Histiocytic vacuolation and hepatocyte necrosis were observed in rats dosed daily at 40 and 80 mg/kg/day, respectively, for 4 weeks, (approximately 3 and 6 times the expected human dose on an exposure basis, respectively). In addition, renal toxicity characterized by increases in serum BUN and creatinine and microscopic kidney findings was observed in rats and dogs at doses 5 to 7 times the expected human dose on an exposure basis. The relationship between these findings in the animal toxicology studies after 28 and 90 consecutive days of dosing to the indicated clinical dosing of 2 doses 7 days apart are unclear.

14 CLINICAL STUDIES

Clinical Studies of DALVANCE in Adult Patients with Acute Bacterial Skin and Skin Structure Infections

DALVANCE Two-dose Regimen (1,000 mg Day 1; 500 mg Day 8)

Adult patients with ABSSSI were enrolled in two Phase 3, randomized, double-blind, double-dummy clinical trials of similar design (Trial 1 and Trial 2). The Intent-to-Treat (ITT) population included 1,312 randomized patients. Patients were treated for two weeks with either a two-dose regimen of intravenous DALVANCE (1,000 mg followed one week later by 500 mg) or intravenous vancomycin (1,000 mg or 15 mg/kg every 12 hours, with the option to switch to oral linezolid after 3 days). DALVANCE-treated patients with creatinine clearance of less than 30 mL/min received 750 mg followed one week later by 375 mg. Approximately 5% of patients also received a protocol-specified empiric course of treatment with intravenous aztreonam for coverage of Gram-negative pathogens.

The specific infections in these trials included cellulitis (approximately 50% of patients across treatment groups), major abscess (approximately 30%), and wound infection (approximately 20%). The median lesion area at baseline was 341 cm^2. In addition to local signs and symptoms of infection, patients were also required to have at least one systemic sign of disease at baseline, defined as temperature 38°C or higher (approximately 85% of patients), white blood cell count greater than 12,000 cells/mm^3 (approximately 40%), or 10% or more band forms on white blood cell differential (approximately 23%). Across both trials, 59% of patients were from Eastern Europe and 36% of patients were from North America. Approximately 89% of patients were Caucasian and 58% were males. The mean age was 50 years and the mean body mass index was 29.1 kg/m^2.

The primary endpoint of these two ABSSSI trials was the clinical response rate where responders were defined as patients who had no increase from baseline in lesion area 48 to 72 hours after initiation of therapy, and had a temperature consistently at or below 37.6°C upon repeated measurement. Table 5 summarizes overall clinical response rates in these two ABSSSI trials using the pre-specified primary efficacy endpoint in the ITT population.

Table 5. Clinical Response Rates in ABSSSI Trials at 48-72 Hours after Initiation of Therapy^1,2
 | DALVANCE n/N (%) | Vancomycin/Linezolid n/N (%) | Difference (95% CI)^3
Trial 1 | 240/288 (83.3) | 233/285 (81.8) | 1.5 (-4.6, 7.9)
Trial 2 | 285/371 (76.8) | 288/368 (78.3) | -1.5 (-7.4, 4.6)

^1 There were 7 patients who did not receive treatment and were counted as non-responders: 6 DALVANCE patients (3 in each trial) and one vancomycin/linezolid patient in Trial 2.

^2 Patients who died or used non-study antibacterial therapy or had missing measurements were classified as non-responders.

^3 The 95% Confidence Interval (CI) is computed using the Miettinen and Nurminen approach, stratified by baseline fever status.

A key secondary endpoint in these two ABSSSI trials evaluated the percentage of ITT patients achieving a 20% or greater reduction in lesion area from baseline at 48-72 hours after initiation of therapy. Table 6 summarizes the findings for this endpoint in these two ABSSSI trials.

Table 6. Patients in ABSSSI Trials with Reduction in Lesion Area of 20% or Greater at 48-72 Hours after Initiation of Therapy^1,2
 | DALVANCE n/N (%) | Vancomycin/Linezolid n/N (%) | Difference (95% CI)^3
Trial 1 | 259/288 (89.9) | 259/285 (90.9) | -1.0 (-5.7, 4.0)
Trial 2 | 325/371 (87.6) | 316/368 (85.9) | 1.7 (-3.2, 6.7)

^1 There were 7 patients (as described in Table 5) who did not receive treatment and were counted as non-responders.

^2 Patients who died or used non-study antibacterial therapy or had missing measurements were classified as non-responders.

^3 The 95% CI is computed using the Miettinen and Nurminen approach, stratified by baseline fever status.

Another secondary endpoint in these two ABSSSI trials was the clinical success rate assessed at a follow-up visit occurring between Days 26 to 30. Clinical Success at this visit was defined as having a decrease in lesion size (both length and width measurements), a temperature of 37.6°C or lower, and meeting pre-specified criteria for local signs: purulent discharge and drainage absent or mild and improved from baseline, heat/warmth & fluctuance absent, swelling/induration & tenderness to palpation absent or mild.

Table 7 summarizes clinical success rates at a follow-up visit for the ITT and clinically evaluable population in these two ABSSSI trials. Note that there are insufficient historical data to establish the magnitude of drug effect for antibacterial drugs compared with placebo at the follow-up visits. Therefore, comparisons of DALVANCE to vancomycin/linezolid based on clinical success rates at these visits cannot be utilized to establish non-inferiority.

Table 7. Clinical Success Rates in ABSSSI Trials at Follow-Up (Day 26 to 30) ^1,2
 | DALVANCE n/N (%) | Vancomycin/Linezolid n/N (%) | Difference (95% CI)^3
Trial 1
ITT | 241/288 (83.7%) | 251/285 (88.1%) | -4.4% (-10.1, 1.4)
CE | 212/226 (93.8%) | 220/229 (96.1%) | -2.3% (-6.6, 2.0)
Trial 2
ITT | 327/371 (88.1%) | 311/368 (84.5%) | 3.6% (-1.3, 8.7)
CE | 283/294 (96.3%) | 257/272 (94.5%) | 1.8% (-1.8, 5.6)

^1 There were 7 patients (as described in Table 5) who did not receive treatment and were counted as failures in the analysis.

^2 Patients who died, used non-study antibacterial therapy, or had an unplanned surgical intervention 72 hours after the start of therapy were classified as Clinical Failures.

^3 The 95% CI is computed using the Miettinen and Nurminen approach, stratified by baseline fever status.

Table 8 shows outcomes in patients with an identified baseline pathogen, using pooled data from Trials 1 and 2 in the microbiological ITT (microITT) population. The outcomes shown in the table are clinical response rates at 48 to 72 hours and clinical success rates at follow-up (Day 26 to 30), as defined above.

Table 8. Outcomes by Baseline Pathogen (Trial 1, 2; MicroITT) ^1
Early Clinical Response at 48-72 hours
 | Early Responder^2 |  | ≥ 20% reduction in lesion size |  | Clinical Success at Day 26 to 30
Pathogen | DALVANCE n/N (%) | Comparator n/N (%) | DALVANCE n/N (%) | Comparator n/N (%) | DALVANCE n/N (%) | Comparator n/N (%)
Staphylococcus aureus Methicillin-susceptible Methicillin-resistant | 206/257 (80.2) 134/167 (80.2) 72/90 (80.0) | 219/256 (85.5) 163/189 (86.2) 56/67 (83.6) | 239/257 (93.0) 156/167 (93.4) 83/90 (92.2) | 232/256 (90.6) 173/189 (91.5) 59/67 (88.1) | 217/257 (84.4) 142/167 (85.0) 75/90 (83.3) | 229/256 (89.5) 171/189 (90.5) 57/67 (85.1)
Streptococcus agalactiae | 6/12 (50.0) | 11/14 (78.6) | 10/12 (83.3) | 10/14 (71.4) | 10/12 (83.3) | 11/14 (78.6)
Streptococcus pyogenes | 28/37 (75.7) | 24/36 (66.7) | 32/37 (86.5) | 27/36 (75.0) | 33/37 (89.2) | 32/36 (88.9)
Streptococcus anginosus group | 18/22 (81.8) | 23/ 25 (92.0) | 21/22 (95.5) | 25/25 (100.0) | 21/22 (95.5) | 23/25 (92.0)
Enterococcus faecalis | 8/12 (66.7) | 10/13 (76.9) | 12/12 (100.0) | 12/13 (92.3) | 12/12 (100.0) | 11/13 (84.6)

All DALVANCE dosing regimens in Trials 1 and 2 consisted of two doses.

^1 There were 2 patients in the DALVANCE arm with methicillin-susceptible S. aureus at baseline who did not receive treatment and were counted as non-responders/failures.

^2 Early Responders are patients who had no increase from baseline in lesion area 48 to 72 hours after initiation of therapy, and had a temperature consistently at or below 37.6°C upon repeated measurement.

DALVANCE 1,500 mg Single Dose Regimen

Adult patients with ABSSSI were enrolled in a Phase 3, double-blind, clinical trial. The ITT population included 698 patients who were randomized to DALVANCE treatment with either a single 1,500 mg dose or a two-dose regimen of 1,000 mg followed one week later by 500 mg (Trial 3). Patients with creatinine clearance less than 30 mL/min had their dose adjusted (Section 2.2). Approximately 5% of patients also received a protocol-specified empiric course of treatment with intravenous aztreonam for coverage of Gram-negative pathogens. The specific infections and other patient characteristics in this trial were similar to those described above for previous ABSSSI trials.

The primary endpoint in this ABSSSI trial was the clinical response rate where responders were defined as patients who had at least a 20% decrease from baseline in lesion area 48 to 72 hours after randomization without receiving any rescue antibacterial therapy. The secondary endpoint was the clinical success rate at a follow-up visit occurring between Days 26 and 30, with clinical success defined as having at least a 90% decrease from baseline in lesion size, a temperature of 37.6°C or lower, and meeting pre-specified criteria for local signs: purulent discharge and drainage absent or mild and improved from baseline (for patients with wound infections), heat/warmth and fluctuance absent, swelling/induration and tenderness to palpation absent or mild. Table 9 summarizes results for these two endpoints in the ITT population. Note that there are insufficient historical data to establish the magnitude of drug effect for antibacterial drugs compared with placebo at the follow-up visit. Therefore, comparisons between treatment groups based on clinical success rates at this visit cannot be utilized to establish non-inferiority.

Table 9. Primary and Secondary Efficacy Results in ABSSSI Patients (Trial 3) ^1,2
 | DALVANCE, n/N (%)
 | Single Dose (1,500 mg) | Two doses (1,000 mg Day 1/500 mg Day 8) | Difference (95% CI)^3
Clinical Responders at 48-72 Hours (ITT) | 284/349 (81.4) | 294/349 (84.2) | -2.9 (-8.5, 2.8)
Clinical Success at Day 26-30 (ITT) | 295/349 (84.5) | 297/349 (85.1) | -0.6 (-6.0, 4.8)
Clinical Success at Day 26-30 (CE) | 250/271 (92.3) | 247/267 (92.5) | -0.3 (-4.9, 4.4)

^1 There were 3 patients in the two-dose group who did not receive treatment and were counted as non-responders.

^2 Patients who died or used non-study antibacterial therapy or had missing measurements were classified as non-responders.

^3 The 95% Confidence Interval (CI) is computed using the Miettinen and Nurminen approach.

Abbreviations: ITT-intent to treat; CE-clinically evaluable

Table 10 shows outcomes in patients with an identified baseline pathogen from Trial 3 in the microbiological ITT (microITT) population. The outcomes shown in the table are clinical response rates at 48 to 72 hours and clinical success rates at follow-up (Day 26 to 30), as defined above.

Table 10. Outcomes by Baseline Pathogen (Trial 3; MicroITT)
Early Clinical Response at 48-72 hours
 | ≥ 20% reduction in lesion size |  | Clinical Success at Day 26 to 30
Pathogen | Single dose (1,500 mg) n/N (%) | Two doses (1,000 mg Day 1/ 500 mg Day 8) n/N (%) | Single dose (1,500 mg) n/N (%) | Two doses (1,000 mg Day 1/ 500 mg Day 8) n/N (%)
Staphylococcus aureus Methicillin-susceptible Methicillin-resistant | 123/139 (88.5) 92/103 (89.3) 31/36 (86.1) | 133/156 (85.3) 89/96 (89.6) 48/61 (78.7) | 124/139 (89.2) 93/103 (90.3) 31/36 (86.1) | 140/156 (89.7) 86/96 (89.6) 55/61 (90.2)
Streptococcus agalactiae | 6/6(100.0) | 4/6 (66.7) | 5/6 (83.3) | 5/6 (83.3)
Streptococcus anginosus group | 31/33 (93.9) | 19/19 (100.0) | 29/33 (87.9) | 17/19 (89.5)
Streptococcus pyogenes | 14/14 (100.0) | 18/22 (81.8) | 13/14 (92.9) | 19/22 (86.4)
Enterococcus faecalis | 4/4 (100.0) | 8/10 (80.0) | 4/4 (100.0) | 9/10 (90.0)

In Trials 1, 2, and 3, all patients had blood cultures obtained at baseline. A total of 40 ABSSSI patients who received DALVANCE had bacteremia at baseline caused by one or more of the following bacteria: 26 S. aureus (21 MSSA and 5 MRSA), 6 S. agalactiae, 7 S. pyogenes, 2 S. anginosus group, and 1 E. faecalis. In patients who received DALVANCE, a total of 34/40 (85%) were clinical responders at 48-72 hours and 32/40 (80%) were clinical successes at Day 26 to 30.

Clinical Study of DALVANCE in Pediatric Patients with Acute Bacterial Skin and Skin Structure Infections

The pediatric trial was a multicenter, open-label, randomized, actively controlled trial (NCT02814916, Trial 4) conducted in pediatric patients 3 months of age to less than 18 years with ABSSSI, not known or expected to be caused exclusively by Gram-negative organisms. Patients were randomized in a 3:3:1 ratio to receive either DALVANCE single-dose regimen, DALVANCE two-dose regimen, or comparator. The comparator regimens included IV vancomycin for methicillin-resistant Gram-positive infections, or IV oxacillin or flucloxacillin for methicillin-susceptible Gram-positive infections. Patients in the comparator arm received IV treatment for a minimum of 72 hours before an optional switch to oral therapy to complete a total of 10-14 days of antibacterial drug therapy. Additional 5 patients from birth to < 3 months of age were enrolled and assigned to the DALVANCE single-dose regimen.

A study population of 191 pediatric patients received study medication (DALVANCE single dose regimen n=83, DALVANCE two-dose regimen n=78, comparator n=30); 62% of the patients were male and 89% were white, and 83% were from Eastern Europe. The pediatric age groups who received DALVANCE were as follows: 12 to < 18 years (n=58), 6 to < 12 years (n=49), 2 to < 6 years (n=35), 3 months to < 2 years (n=14), and birth < 3 months (n=5). Patients had diagnoses of major cutaneous abscess (53%), cellulitis (29%), or surgical site/traumatic wound infection (18%). The predominant pathogen at baseline was Staphylococcus aureus (84%).

The primary objective was to evaluate the safety and tolerability of DALVANCE. The trial was not powered for a comparative inferential efficacy analysis. Efficacy was assessed in the modified intent-to-treat population (n=183) which included all randomized patients who received any dose of study drug and had a diagnosis of ABSSSI caused by Gram-positive organism(s). Patients with ABSSSI only caused by Gram-negative organisms were excluded. The five patients in the age group birth to < 3 months of age were not included in efficacy analyses since they were enrolled with expanded inclusion criteria and only received the single dose DALVANCE regimen. An early clinical response at 48–72 hours was defined as ≥ 20% reduction in lesion size compared to baseline and no receipt of rescue antibacterial therapy. The proportion of patients with early clinical response, was 97.3% (73/75) in the DALVANCE single-dose arm, 93.6% (73/78) in the DALVANCE two-dose arm, and 86.7% (26/30) in the comparator arm. The difference in responder rates between the dalbavancin single-dose and comparator arms was 10.7%, with an exact 97.5% confidence interval (CI) of (-1.7%, 31.6%). The difference in responder rates between the dalbavancin two-dose and comparator arms was 6.9%, with an exact 97.5% CI of (-6.4%, 27.7%).

Clinical cure was defined as resolution of the clinical signs and symptoms of infection, when compared to baseline, and no additional antibacterial treatment for the disease under study. In patients, 3 months of age or older in the mITT population, the clinical cure rate at the test of cure (TOC) visit (28 ± 2 days) was 94.7% (71/75) in the DALVANCE single-dose arm, 92.3% (72/78) in the DALVANCE two-dose arm and 100% (30/30) in the comparator arm. The difference in cure rates between the dalbavancin single-dose and comparator arms was -5.3%, with an exact 97.5% CI of (-15.1%, 10.5%). The difference in cure rates between the dalbavancin two-dose and comparator arms was -7.7%, with an exact 97.5% CI of (-17.9%, 8.3%).

16 HOW SUPPLIED/STORAGE AND HANDLING

DALVANCE (dalbavancin) for injection is supplied as a white/off-white to pale yellow sterile lyophilized powder in a single-dose glass vial containing dalbavancin hydrochloride equivalent to 500 mg dalbavancin:

Package of 1 individual vial (500 mg/vial) in carton: (NDC 57970-100-01)

DALVANCE (dalbavancin) for injection should be stored at 25ºC (77ºF); excursions permitted to 15ºC to 30ºC (59ºF to 86ºF) [see USP Controlled Room Temperature]. Storage of the reconstituted and diluted solutions of DALVANCE are described elsewhere in the prescribing information [see Dosage and Administration (2.4)].

17 PATIENT COUNSELING INFORMATION

Allergic Reactions

Advise patients that allergic reactions, including serious allergic reactions, could occur with DALVANCE, and that serious allergic reactions require immediate treatment. Patients should inform their healthcare provider about any previous hypersensitivity reactions to DALVANCE, or other glycopeptides [see Warnings and Precautions (5.1)].

Diarrhea

Advise patients that diarrhea is a common problem caused by antibacterial drugs, including DALVANCE, and usually resolves when the drug is discontinued. Sometimes, frequent watery or bloody diarrhea may occur and may be a sign of a more serious intestinal infection. If severe watery or bloody diarrhea develops, patients should contact their healthcare provider [see Warnings and Precautions (5.4)].

Development of Drug-Resistant Bacteria

Patients should be counseled that antibacterial drugs including DALVANCE should only be used to treat bacterial infections. They do not treat viral infections (e.g., the common cold). When DALVANCE is prescribed to treat a bacterial infection, patients should be told that although it is common to feel better early in the course of therapy, the medication should be taken exactly as directed. Skipping doses or not completing the full course of therapy may (1) decrease the effectiveness of the immediate treatment, and (2) increase the likelihood that bacteria will develop resistance and will not be treatable by DALVANCE or other antibacterial drugs in the future [see Warnings and Precautions (5.5)].

Distributed by:
AbbVie Inc.
North Chicago, IL 60064

DALVANCE and its design are trademarks of Allergan Pharmaceuticals International Limited, an AbbVie company.

© 2025 AbbVie. All rights reserved.

PAA234914

PRINCIPAL DISPLAY PANEL

NDC 57970-100-01
Rx Only
DALVANCE®
(dalbavancin) for injection
500 mg per vial
For Intravenous Infusion Only
Sterile Single-Dose Vial
Discard Unused Portion
abbvie
One Vial